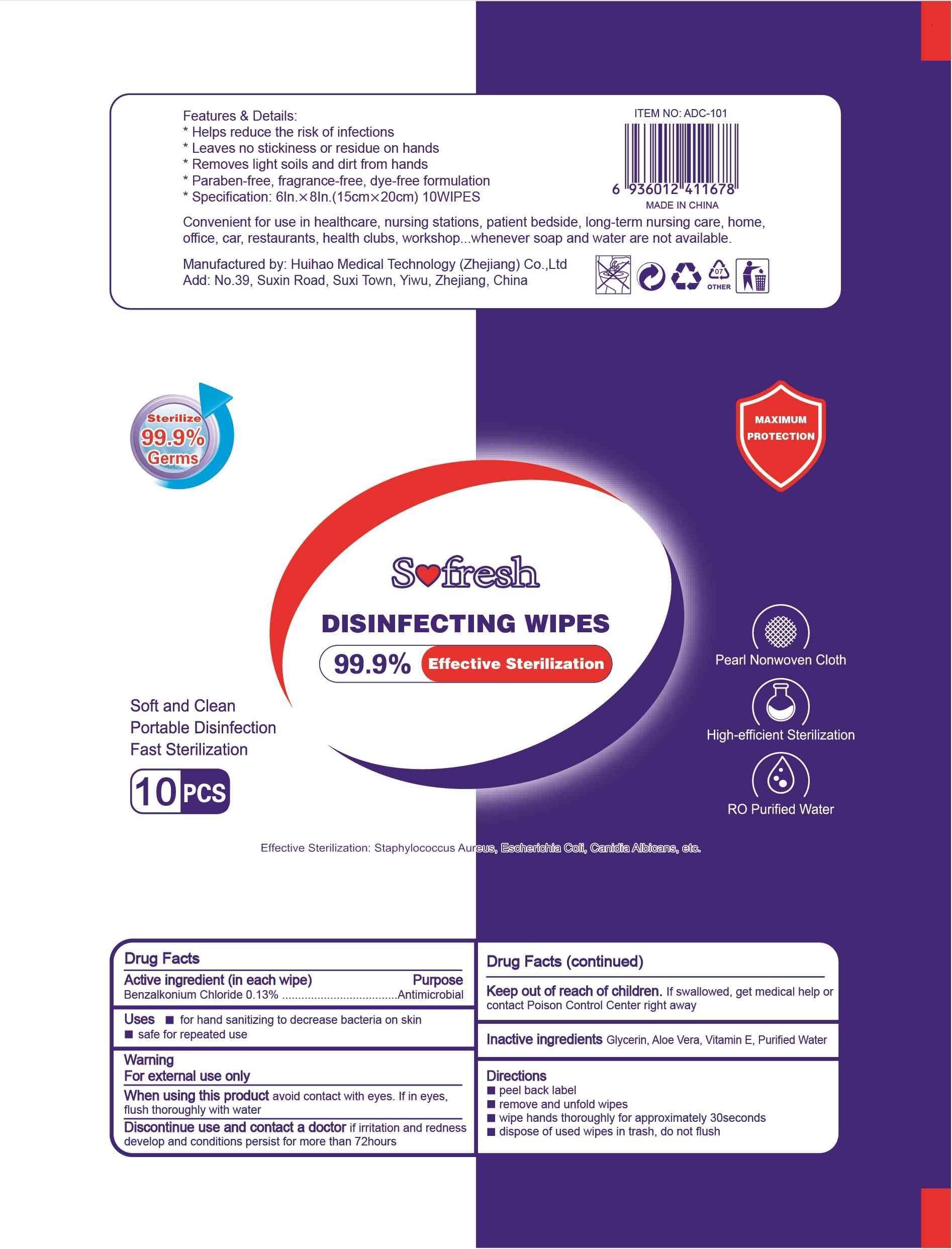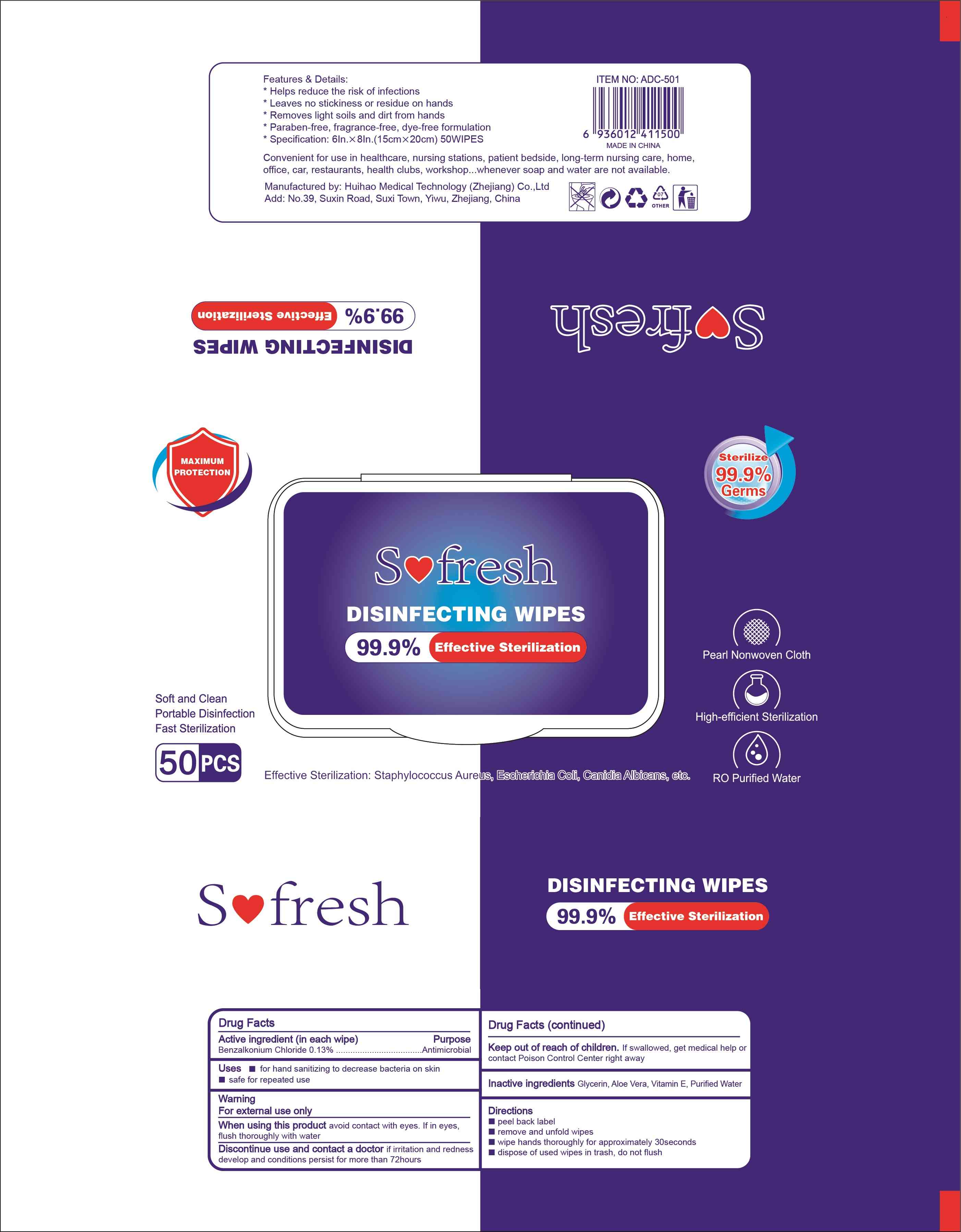 DRUG LABEL: Wipes
NDC: 77909-010 | Form: CLOTH
Manufacturer: Huihao Medical Technology (Zhejiang) Co., Ltd
Category: otc | Type: HUMAN OTC DRUG LABEL
Date: 20201124

ACTIVE INGREDIENTS: BENZALKONIUM CHLORIDE 0.13 g/100 1
INACTIVE INGREDIENTS: GLYCERIN; ALPHA-TOCOPHEROL; WATER

77909-010
Wipes

Active Ingredient(s)

Benzalkoniu m Chlloridle O.13%

Use

for hand sanitizing to decrease bacteria on skin
safe for repeated use

Warnings

For exter1nal use onlly

Do not use

/

WHEN USING

When using this p1rodlu1ct avoid contact with eyes. If in1e yes, flush thoroughly with water

STOP USE

Discontinue use and contact a doctor if irritation and redness develop and conditions persist for more than 72hours

Keep out of reach of children. If swallowed, get medical help or contact Poison Control Center right away

Directions

peel back label
remove and un1fold wipes
wipe hands thoroughly for approximately 30seconds
dispose of used wipes in trash, do not flush.

Other information

/

Inactive ingredients

Glycerin, Aloe Vera, Vitamin E, Purified Water